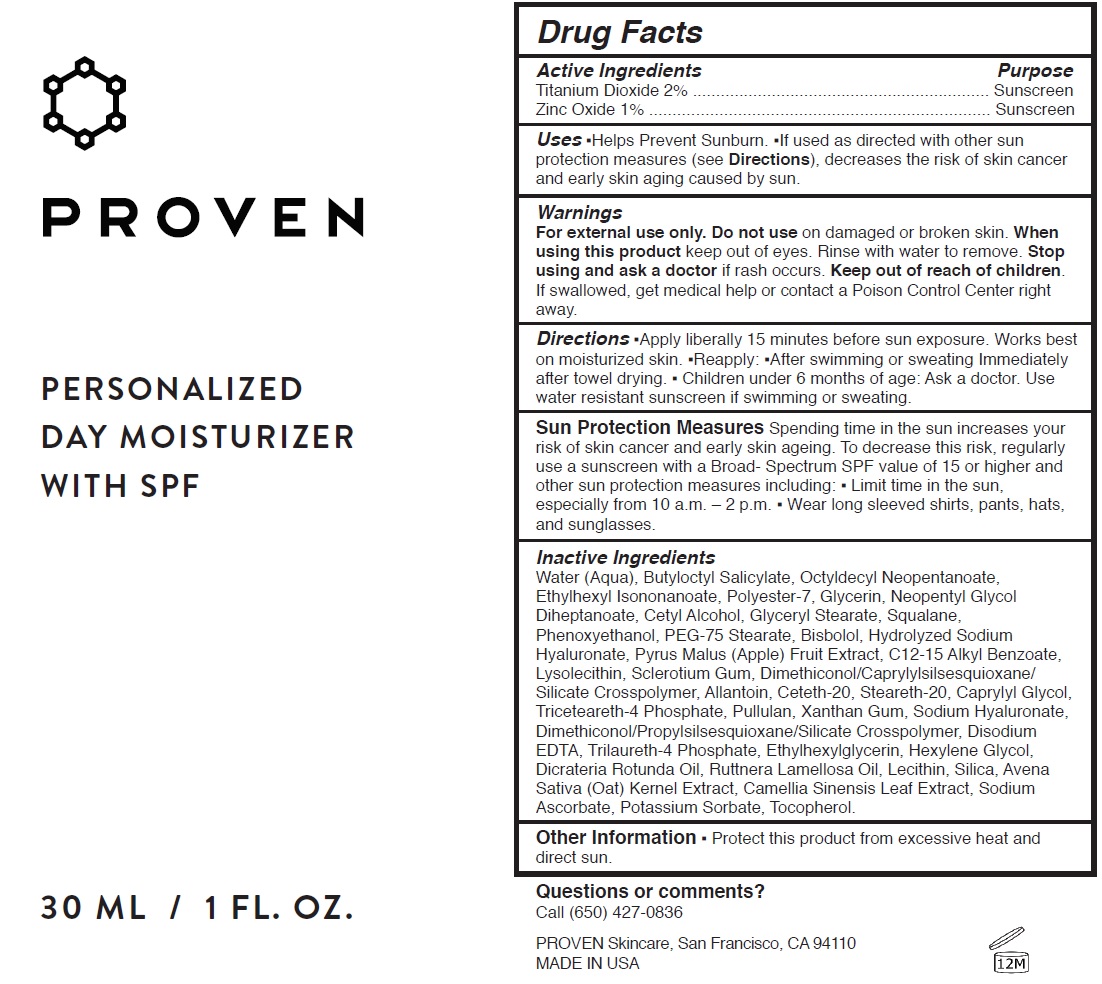 DRUG LABEL: Personalized Day Moisturizer with SPF
NDC: 73572-002 | Form: CREAM
Manufacturer: Proven Skincare
Category: otc | Type: HUMAN OTC DRUG LABEL
Date: 20231110

ACTIVE INGREDIENTS: TITANIUM DIOXIDE 20 mg/1 mL; ZINC OXIDE 10 mg/1 mL
INACTIVE INGREDIENTS: WATER; BUTYLOCTYL SALICYLATE; ETHYLHEXYL ISONONANOATE; POLYESTER-7; GLYCERIN; NEOPENTYL GLYCOL DIHEPTANOATE; CETYL ALCOHOL; GLYCERYL MONOSTEARATE; SQUALANE; PHENOXYETHANOL; PEG-75 STEARATE; APPLE; ALKYL (C12-15) BENZOATE; LYSOPHOSPHATIDYLCHOLINE, SOYBEAN; BETASIZOFIRAN; ALLANTOIN; CETETH-20; STEARETH-20; CAPRYLYL GLYCOL; TRICETEARETH-4 PHOSPHATE; PULLULAN; XANTHAN GUM; HYALURONATE SODIUM; DIMETHICONOL/PROPYLSILSESQUIOXANE/SILICATE CROSSPOLYMER (450000000 MW); EDETATE DISODIUM ANHYDROUS; TRILAURETH-4 PHOSPHATE; ETHYLHEXYLGLYCERIN; HEXYLENE GLYCOL; DICRATERIA ROTUNDA OIL; RUTTNERA LAMELLOSA OIL; SILICON DIOXIDE; OAT; GREEN TEA LEAF; SODIUM ASCORBATE; POTASSIUM SORBATE; TOCOPHEROL

Personalized Day Moisturizer with SPF (40)

Active Ingredients

Titanium Dioxide 2%

Zinc Oxide 1%

Purpose

Sunscreen

Uses

- Helps Prevent Sunburn.
- If used as directed with other sun protection measures (see Directions), decreases the risk of skin cancer and early skin aging caused by sun.

Warnings

For external use only.

Do not use

on damaged or broken skin.

When using this product

keep out of eyes. Rinse with water to remove.

Stop using and ask a doctor

if rash occurs.

Keep out of reach of children.

If swallowed, get medical help or contact a Poison Control Center right away.

Directions

- Apply liberally 15 minutes before sun exposure. Works best on moisturized skin.
- Reapply:
- After swimming or sweating Immediately after towel drying.
- Children under 6 months of age: Ask a doctor. Use water resistant sunscreen if swimming or sweating.

- Limit time in the sun, especially from 10 a.m. – 2 p.m.
- Wear long sleeved shirts, pants, hats, and sunglasses.

Spending time in the sun increases your risk of skin cancer and early skin ageing. To decrease this risk, regularly use a sunscreen with a Broad- Spectrum SPF value of 15 or higher and other sun protection measures including: Sun Protection Measures

Inactive Ingredients

Water (Aqua), Butyloctyl Salicylate, Octyldecyl Neopentanoate, Ethylhexyl Isononanoate, Polyester-7, Glycerin, Neopentyl Glycol Diheptanoate, Cetyl Alcohol, Glyceryl Stearate, Squalane, Phenoxyethanol, PEG-75 Stearate, Bisbolol, Hydrolyzed Sodium Hyaluronate, Pyrus Malus (Apple) Fruit Extract, C12-15 Alkyl Benzoate, Lysolecithin, Sclerotium Gum, Dimethiconol/Caprylylsilsesquioxane/ Silicate Crosspolymer, Allantoin, Ceteth-20, Steareth-20, Caprylyl Glycol, Triceteareth-4 Phosphate, Pullulan, Xanthan Gum, Sodium Hyaluronate, Dimethiconol/Propylsilsesquioxane/Silicate Crosspolymer, Disodium EDTA, Trilaureth-4 Phosphate, Ethylhexylglycerin, Hexylene Glycol, Dicrateria Rotunda Oil, Ruttnera Lamellosa Oil, Lecithin, Silica, Avena Sativa (Oat) Kernel Extract, Camellia Sinensis Leaf Extract, Sodium Ascorbate, Potassium Sorbate, Tocopherol.

Other Information

- Protect this product from excessive heat and direct sun.